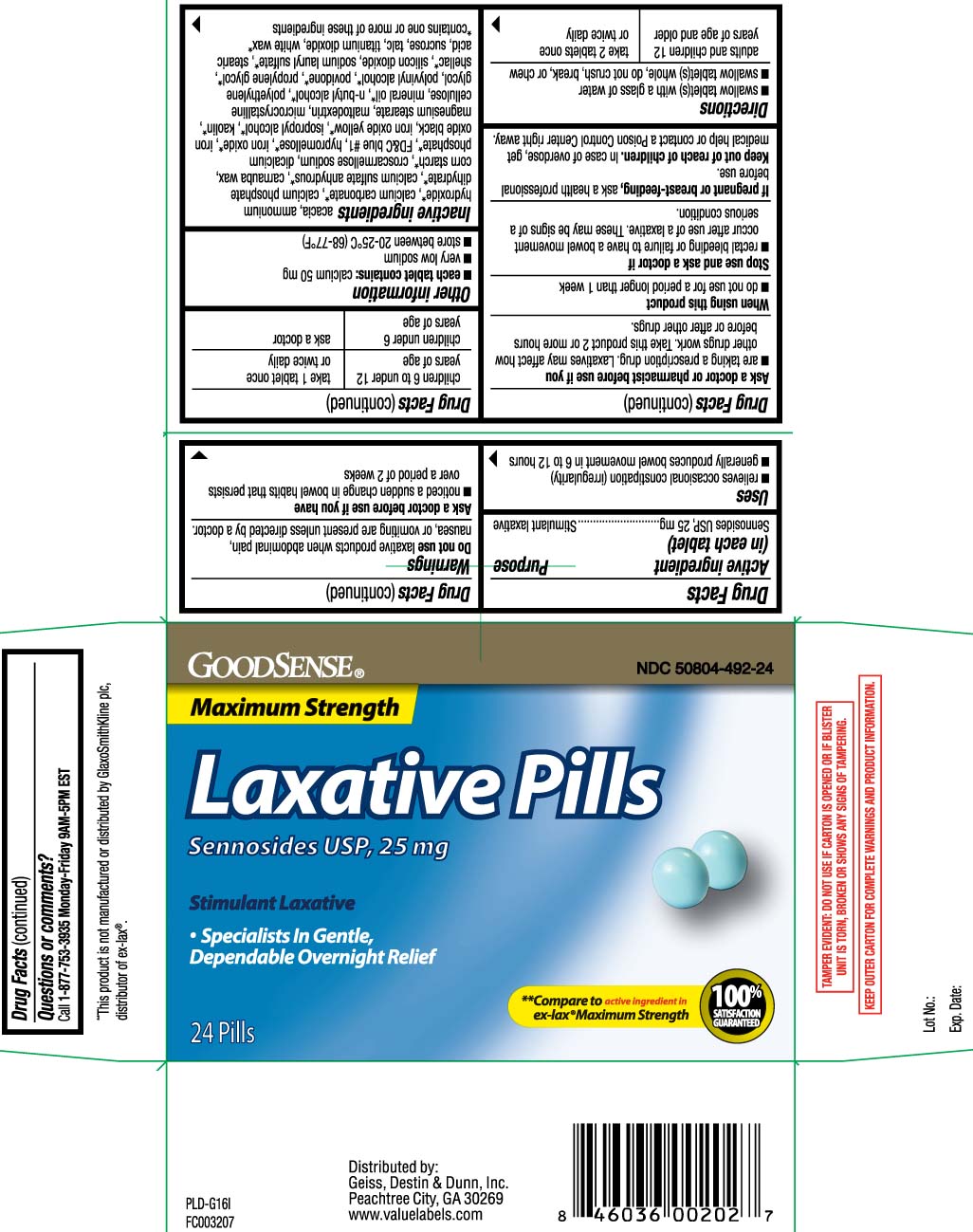 DRUG LABEL: Laxative pills
NDC: 50804-492 | Form: TABLET
Manufacturer: Good Sense (Geiss, Destin & Dunn, Inc.)
Category: otc | Type: HUMAN OTC DRUG LABEL
Date: 20221028

ACTIVE INGREDIENTS: SENNOSIDES 25 mg/1 1
INACTIVE INGREDIENTS: ACACIA; AMMONIA; CALCIUM CARBONATE; CALCIUM PHOSPHATE, DIBASIC, DIHYDRATE; CALCIUM SULFATE ANHYDROUS; CARNAUBA WAX; STARCH, CORN; CROSCARMELLOSE SODIUM; CALCIUM PHOSPHATE, DIBASIC, ANHYDROUS; FD&C BLUE NO. 1; ALUMINUM OXIDE; HYPROMELLOSES; FERRIC OXIDE RED; FERROSOFERRIC OXIDE; FERRIC OXIDE YELLOW; ISOPROPYL ALCOHOL; KAOLIN; MAGNESIUM STEARATE; CELLULOSE, MICROCRYSTALLINE; BUTYL ALCOHOL; POLYETHYLENE GLYCOL, UNSPECIFIED; POVIDONE; PROPYLENE GLYCOL; SHELLAC; SILICON DIOXIDE; SODIUM LAURYL SULFATE; STEARIC ACID; SUCROSE; TALC; TITANIUM DIOXIDE; WHITE WAX; MALTODEXTRIN; MINERAL OIL; POLYVINYL ALCOHOL, UNSPECIFIED

Drug Facts

Active ingredient (in each tablet)

Sennosides USP, 25 mg

Purpose

Stimulant laxative

Uses

- relieves occasional constipation (irregularity)
- generally produces bowel movement in 6 to 12 hours

Warnings

Do not use

laxative products when abdominal pain, nausea, or vomiting are present unless directed by a doctor.

Ask a doctor before use if you have

- noticed a sudden change in bowel habits that persists over a period of 2 weeks

Ask a doctor or pharmacist before use if you

- are taking a prescription drug. Laxatives may affect how other drugs work. Take this product 2 or more hours before or after other drugs.

When using this producct

- do not use for a period longer than 1 week

Stop use and ask a doctor if

- rectal bleeding or failure to have a bowel movement occur after use of a laxative

These may be signs of a serious condition.

If pregnant or breast-feeding,

ask a health professional before use.

Keep out of reach of children.

In case of overdose, get medical help or contact a Poison Control Center right away.

Directions

- swallow tablet(s) with a glass of water
- swallow tablet(s) whole, do not crush, break, or chew

adults and children 12 years of age and older | take 2 tablets once or twice daily
children 6 to under 12 years of age | take 1 tablet once or twice daily
children under 6 years of age | ask a doctor

Other information

- each tablet contains: calcium 50 mg
- very low sodium
- store between 20-25ºC (68-77ºF)

Inactive ingredients

acacia, ammonium hydroxide*, calcium carbonate*, calcium phosphate dihydrate*, calcium sulfate anhydrous*, carnauba wax, corn starch*, croscarmellose sodium, dicalcium phosphate*, FD&C blue #1 aluminum lake, hypromellose*, iron oxide*, iron oxide black, iron oxide yellow*, isopropyl alcohol*, kaolin*, magnesium stearate, maltodextrin, microcrystalline cellulose, mineral oil, n-butyl alcohol*, polyethylene glycol, polyvinyl alcohol*, povidone*, propylene glycol*, shellac, silicon dioxide*, sodium lauryl sulfate*, stearic acid*, sucrose, talc, titanium dioxide, white wax*

*contains one or more of these ingredients

Questions or comments?

Call 1-877-753-3935 Monday-Friday 9AM-5PM EST

Principal Display Panel

Maximum Strength

Laxative pills

Sennosides USP, 25 mg

Stimulant Laxative

- Specialists In Gentle, Dependable Overnight Relief

PILLS

**Compare to active ingredient in ex-lax® Maximum Strength

**This product is not manufactured or distributed by GlaxoSmithKline plc, distributor of Ex-Lax®.

TAMPER EVIDENT: DO NOT USE IF CARTON IS OPENED OR IF BLISTER UNIT IS TORN, BROKEN OR SHOWS ANY SIGNS OF TAMPERING.

KEEP OUTER CARTON FOR COMPLETE WARNINGS AND PRODUCT INFORMATION.

Distributed by:

Geiss, Destin & Dunn, Inc.

Peachtree City, GA 30269

www.valuelabels.com

Product Label

GOODSENSE Laxative Pills